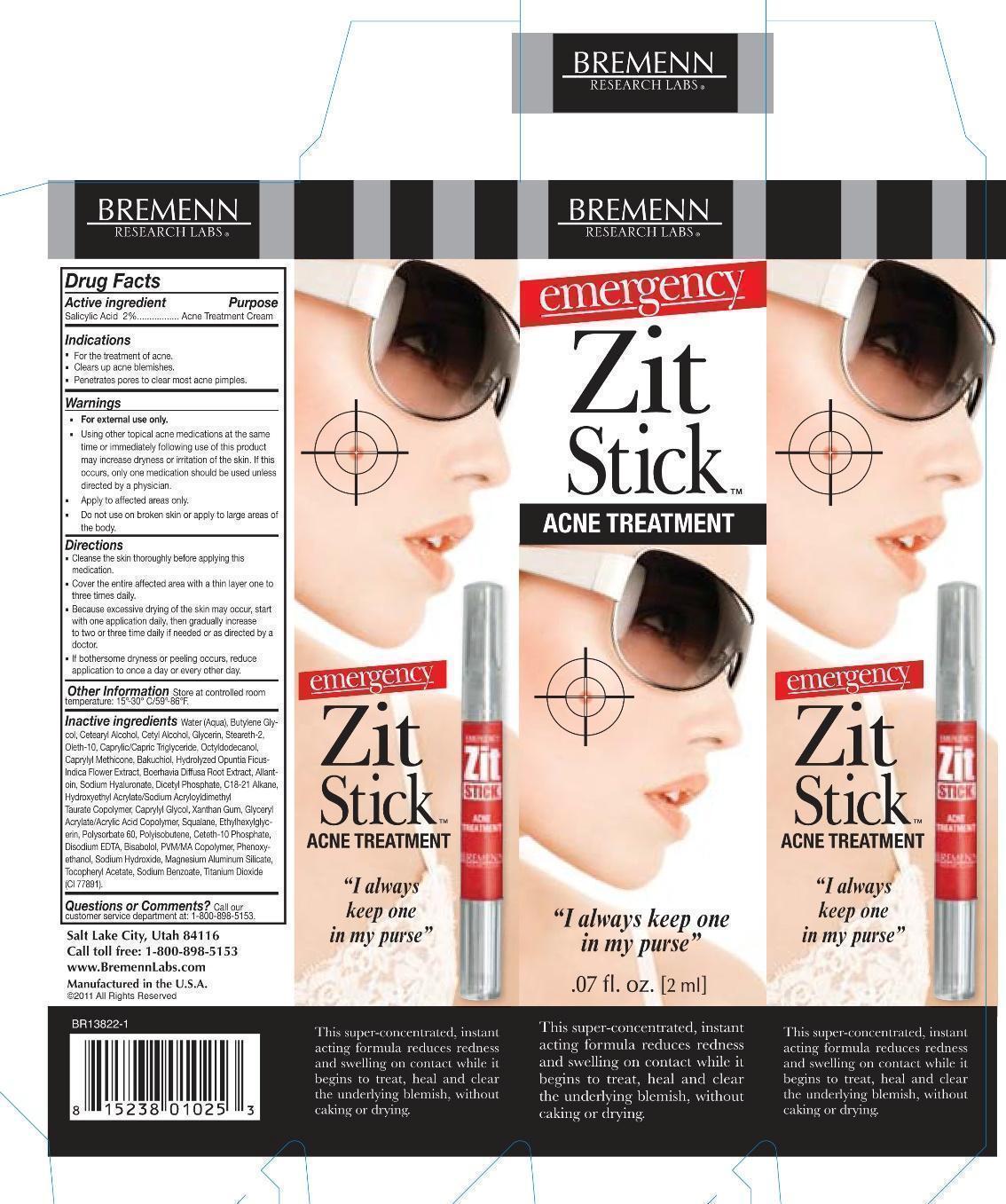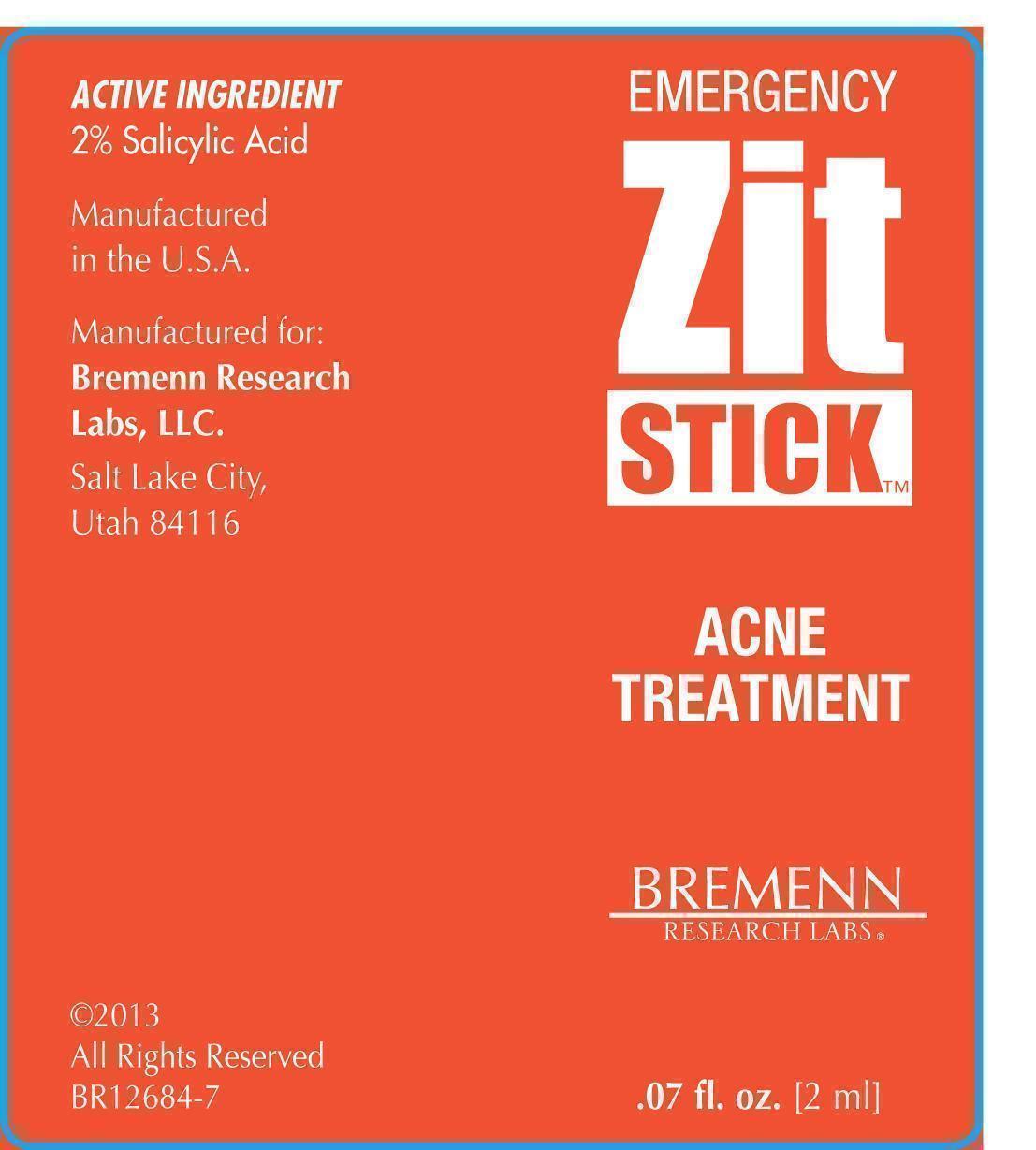 DRUG LABEL: Emergency Zit Treatment
NDC: 61084-125 | Form: STICK
Manufacturer: Basic Research
Category: otc | Type: HUMAN OTC DRUG LABEL
Date: 20150417

ACTIVE INGREDIENTS: SALICYLIC ACID 2 g/100 mL
INACTIVE INGREDIENTS: WATER; BUTYLENE GLYCOL; CETOSTEARYL ALCOHOL; CETYL ALCOHOL; GLYCERIN; STEARETH-2; OLETH-10; MEDIUM-CHAIN TRIGLYCERIDES; OCTYLDODECANOL; CAPRYLYL TRISILOXANE; BAKUCHIOL; ALLANTOIN; HYALURONATE SODIUM; DIHEXADECYL PHOSPHATE; C18-C21 ALKANE; HYDROXYETHYL ACRYLATE/SODIUM ACRYLOYLDIMETHYL TAURATE COPOLYMER (45000 MPA.S AT 1%); CAPRYLYL GLYCOL; XANTHAN GUM; SQUALANE; ETHYLHEXYLGLYCERIN; POLYSORBATE 60; POLYISOBUTYLENE (1300 MW); CETETH-10 PHOSPHATE; EDETATE DISODIUM; LEVOMENOL; PHENOXYETHANOL; SODIUM HYDROXIDE; MAGNESIUM ALUMINUM SILICATE; .ALPHA.-TOCOPHEROL ACETATE; SODIUM BENZOATE; TITANIUM DIOXIDE

Emergency Zit Stick Treatment

Active ingredient Purpose

Salicylic Acid 2% Acne Treatment Cream

Uses

Treats acne

Clears up acne blemishes

Penetrates Pores to clear most acne pimples

Keep out of reach of children. If swallowed get medical or contact a Poison Control Center right away. If swallowed get medical help or contact a poison control center right away.

Do not use on broken skin or apply to large areas of the body

Warnings

For external use only

Using other topical acne medications at the same time or immediately following use of this product may increase dryness or irritation of the skin. if this occurs only one medication should be used unless directed by a physician.

Apply to effected areas only

Directions

Cleanse the skin thoroughly before applying this medication.

Cover the entire affected area with a thin layer one to three times daily.

Because excessive drying of the skin may occur, start with one application daily, then gradually increase to two or three time daily if needed or as directed by a doctor.

If bothersome dryness or peeling occurs, reduce application to once a day or every other day.

Inactive ingredients

Water (Aqua), Butylene Glycol, Cetearyl Alcohol, Cetyl Alcohol, Glycerin, Steareth-2, Oleth-10, Caprylic/Capric Triglyceride, Octyldodecanol, Caprylyl Methicone,Bakuchiol, Hydrolyzed Optunia Ficus-Indica Flower Extract, Boerhavia Diffusia Root Extract, Allantoin, Sodium Hyaluronate, Dicetyl Phophate, C18-21 Alkane, Hydroxyethyl Acrylate/sodium Acryloyldimethyl Taurate Copolymer, Caprylyl Glycol, Xanthan Gum, Glyceryl Acrylate/Acrylic Acid Copolymer, Squalane, Ethylhexylglycerin, Polysorbate 60, Polyisobutene, Ceteth-10 Phosphate, Disodium EDTA, Bisabolol, PVM/MA Copolymer, Phenoxyethanol, Sodium Hydroxide, Magnesium Aluminum Silicate, Tocopheryl Acetate, Sodium Benzoate, Titanium Dioxide (CI 77891)

PACKAGE LABEL

Emergency Zit StickTM
Acne Treatment

" I always keep one in my purse"

.07 fl.oz. [2 ml]